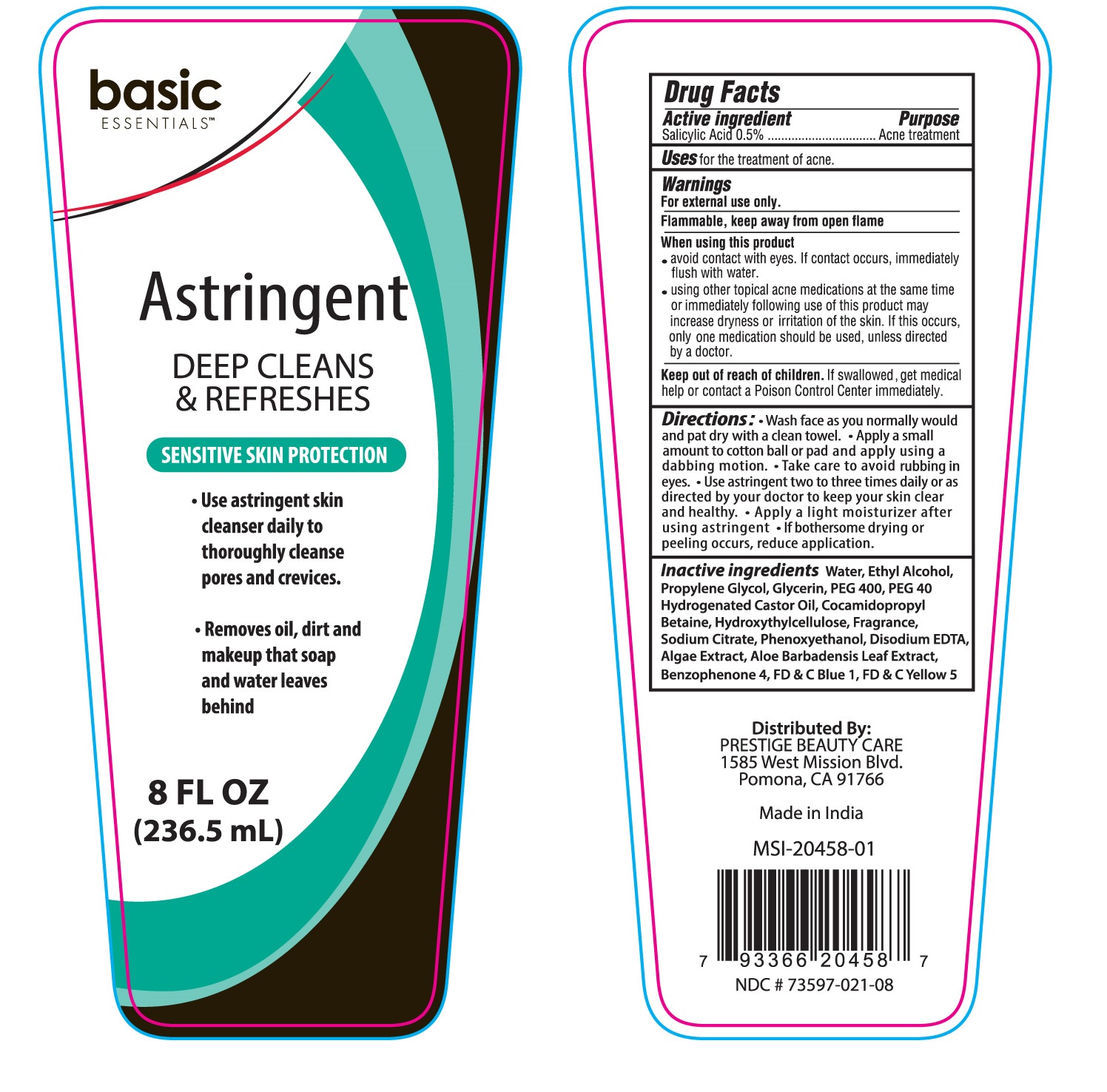 DRUG LABEL: Basic Essentials Astringent
NDC: 73597-021 | Form: SOLUTION
Manufacturer: Mission Series Inc. dpa Prestige Beauty Care
Category: otc | Type: HUMAN OTC DRUG LABEL
Date: 20250108

ACTIVE INGREDIENTS: SALICYLIC ACID 0.05 g/100 mL
INACTIVE INGREDIENTS: GLYCERIN; HYDROXYETHYL CELLULOSE, UNSPECIFIED; SODIUM CITRATE; WATER; BENZOPHENONE; SULISOBENZONE; FD&C BLUE NO. 1; EDETATE DISODIUM ANHYDROUS; ALOE VERA LEAF; POLYETHYLENE GLYCOL 400; PHENOXYETHANOL; FD&C YELLOW NO. 5; ALCOHOL; PROPYLENE GLYCOL; POLYOXYL 40 HYDROGENATED CASTOR OIL; COCAMIDOPROPYL BETAINE

Basic Essentials Astringent

Purpose

Acne Treatment

Active Ingredient

Active Ingredients

Salicylic Acid 0.5%

Indications & Usage

Uses: for the treatment of acne.

Warnings

For external use only.

Flammable, keep away from open flame.

When using this product

• avoid contact with the eyes. If contact occurs, immediately flush thoroughly with water.

Ask a doctor

• using other topical acne medications at the same time or immediately following use of this product may increase dryness or irritation of the skin. If this occurs, only one medication should be used, unless directed by a doctor.

Keep out of reach of children. If swallowed, get medical help or contact a Poison Control Center immediately.

Directions

Directions: • Wash face as you normally would and pat dry with a clean towel. • Apply a small amount to cotton ball or pad and apply using a dabbing motion. • Take care to avoid rubbing in eyes. • Use astringent two to three times daily or as directed by your doctor to keep your skin clear and healthy. • Apply a light moisturizer after using astringent. • If bothersome drying or peeling occurs, reduce application.

Inactive Ingredients

Inactive ingredients Water, Ethyl Alcohol, Propylene Glycol, Glycerin, PEG 400, PEG 40 Hydrogenated Castor Oil, Cocamidopropyl Betaine, Hydroxythylcellulose, Fragrance, Sodium Citrate, Phenoxyethanol, Disodium EDTA, Algae Extract, Aloe Barbadensis Leaf Extract, Benzophenone 4, FD & C Blue 1, FD & C Yellow 5

Distributed by

PRESTIGE BEAUTY CARE

1585 West Mission Blvd.

Pomona, CA 91766

Made in India